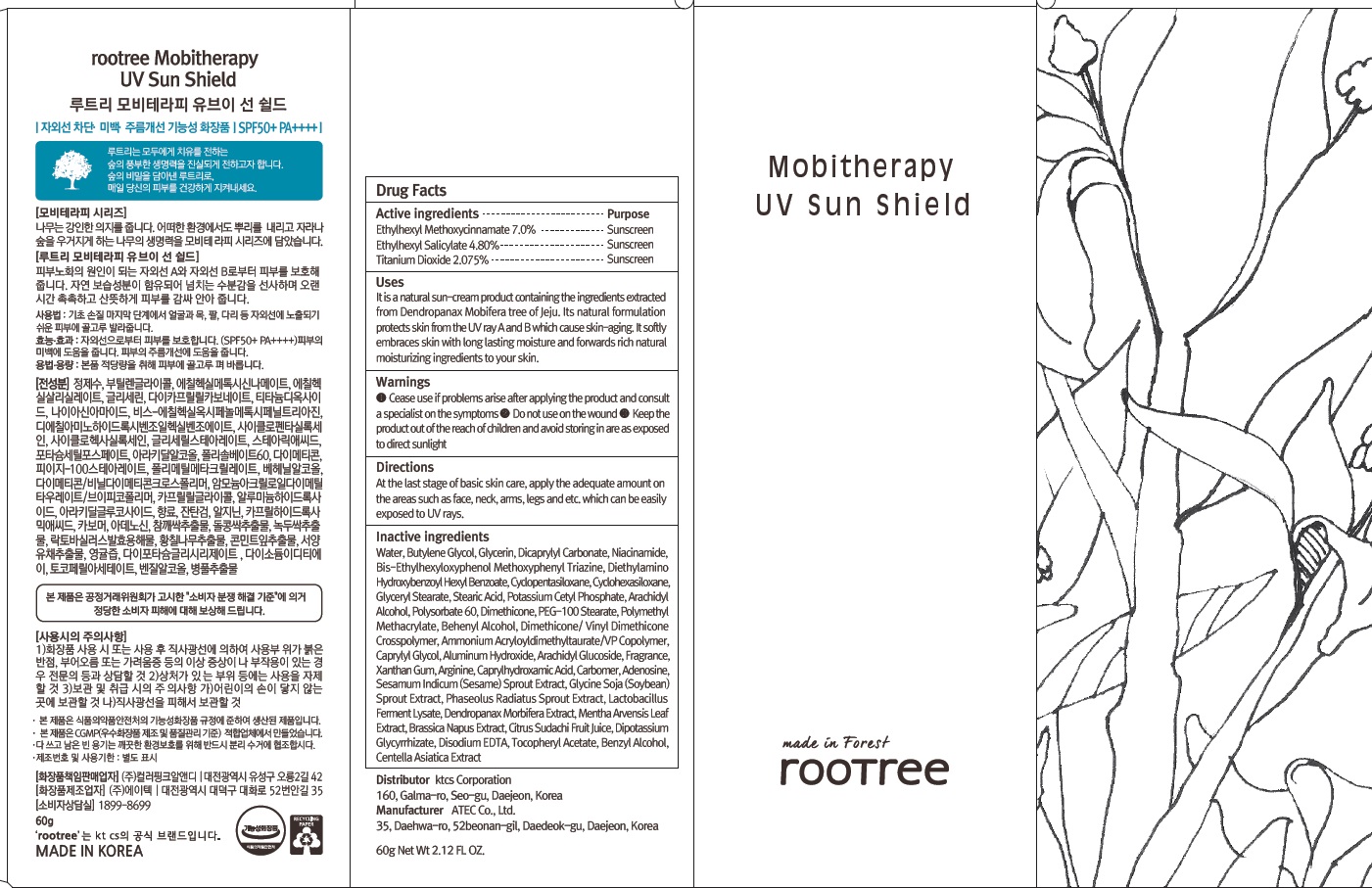 DRUG LABEL: rootree Mobitherapy UV Sun Shield
NDC: 72441-070 | Form: CREAM
Manufacturer: KTCS Corporation
Category: otc | Type: HUMAN OTC DRUG LABEL
Date: 20201231

ACTIVE INGREDIENTS: Octinoxate 4.2 g/60 g; Octisalate 2.88 g/60 g; Titanium Dioxide 1.24 g/60 g
INACTIVE INGREDIENTS: Water; Butylene Glycol

ACTIVE INGREDIENTS

Ethylhexyl Methoxycinnamate 7.0%
Ethylhexyl Salicylate 4.80%
Titanium Dioxide 2.075%

INACTIVE INGREDIENTS

Water, Butylene Glycol, Glycerin, Dicaprylyl Carbonate, Niacinamide, Bis-Ethylhexyloxyphenol Methoxyphenyl Triazine, Diethylamino Hydroxybenzoyl Hexyl Benzoate, Cyclopentasiloxane, Cyclohexasiloxane, Glyceryl Stearate, Stearic Acid, Potassium Cetyl Phosphate, Arachidyl Alcohol, Polysorbate 60, Dimethicone, PEG-100 Stearate, Polymethyl Methacrylate, Behenyl Alcohol, Dimethicone/ Vinyl Dimethicone Crosspolymer, Ammonium Acryloyldimethyltaurate/VP Copolymer, Caprylyl Glycol, Aluminum Hydroxide, Arachidyl Glucoside, Fragrance, Xanthan Gum, Arginine, Caprylhydroxamic Acid, Carbomer, Adenosine, Sesamum Indicum (Sesame) Sprout Extract, Glycine Soja (Soybean) Sprout Extract, Phaseolus Radiatus Sprout Extract, Lactobacillus Ferment Lysate, Dendropanax Morbifera Extract, Mentha Arvensis Leaf Extract, Brassica Napus Extract, Citrus Sudachi Fruit Juice, Dipotassium Glycyrrhizate, Disodium EDTA, Tocopheryl Acetate, Benzyl Alcohol, Centella Asiatica Extract

PURPOSE

Sunscreen

WARNINGS

- Cease use if problems arise after applying the product and consult a specialist on the symptoms

- Do not use on the wound

- Keep the product out of the reach of children and avoid storing in are as exposed to direct sunlight

DESCRIPTION

Uses:

It is a natural sun-cream product containing the ingredients extracted from Dendropanax Mobifera tree of Jeju. Its natural formulation protects skin from the UV ray A and B which cause skin-aging. It softly embraces skin with long lasting moisture and forwards rich natural moisturizing ingredients to your skin.

Directions:

At the last stage of basic skin care, apply the adequate amount on the areas such as face, neck, arms, legs and etc. which can be easily exposed to UV rays.